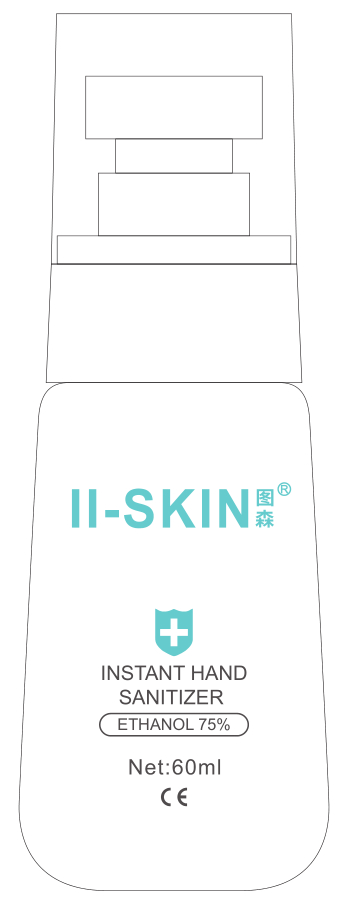 DRUG LABEL: Instant Hand Sanitizer (Ethanol 75%)
NDC: 53074-004 | Form: GEL
Manufacturer: ZHEJIANG ANJI HUABU INDUSTRIAL CO., LTD
Category: otc | Type: HUMAN OTC DRUG LABEL
Date: 20200529

ACTIVE INGREDIENTS: ALCOHOL 45 mL/60 mL
INACTIVE INGREDIENTS: ALOE VERA LEAF; CARBOMER INTERPOLYMER TYPE A (55000 CPS); EDETOL; GLYCERIN; WATER

DOSAGE AND ADMINISTRATION

Keep away from light and store in a cool, dry and ventilated place.

INACTIVE INGREDIENT

Aloe Barbadensis Leaf Extract、Acrylates / C10-30 Alkyl Acrylate Crosspolymer、Tetrahydroxypropyl Ethylenediamine、Glycerol、Aqua

INDICATIONS AND USAGE

Apply an appropriate amount of the product evenly on the hands,faces and skin of other necessary parts of the body, gently rub and massage until it is absorbed.

ACTIVE INGREDIENT

Ethanol

keep out of reach of children

PURPOSE

Disinfection
Sterilization
No Rinseing

WARNINGS

1. This product is a topical disinfectant and should not be taken orally.
2. Place the product out of reach of children.
3. Inflammable, keep away from fire source.
4. Store the product in a cool, dark and dry place.
5. This product is not suitable for disinfection of fat-soluble surfaces.